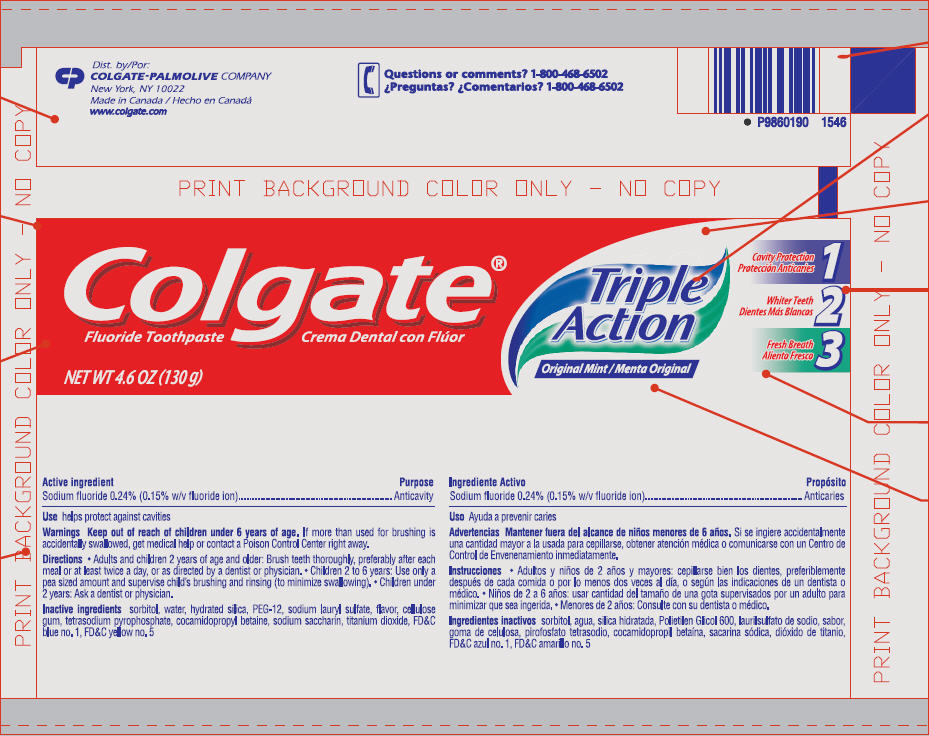 DRUG LABEL: Colgate Triple Action Original Mint Fluoride
NDC: 51442-536 | Form: PASTE, DENTIFRICE
Manufacturer: Colgate-Palmolive Canada
Category: otc | Type: HUMAN OTC DRUG LABEL
Date: 20101118

ACTIVE INGREDIENTS: Sodium Fluoride 2.4 mg/1 g
INACTIVE INGREDIENTS: Sorbitol; Water; Hydrated Silica; Polyethylene Glycol; Sodium Lauryl Sulfate; Carboxymethylcellulose Sodium; Sodium Pyrophosphate; Cocamidopropyl Betaine; Saccharin Sodium; Titanium Dioxide; FD&C Blue No. 1; FD&C YELLOW NO. 5

Colgate®
Triple
Action
Original Mint

Active ingredient

Sodium fluoride 0.24% (0.15% w/v fluoride ion)

Purpose

Anticavity

Use

helps protect against cavities

Warnings

Keep out of reach of children under 6 years of age. If more than used for brushing is accidentally swallowed, get medical help or contact a Poison Control Center right away.

Directions

- Adults and children 2 years of age and older: Brush teeth thoroughly, preferably after each meal or at least twice a day, or as directed by a dentist or physician.
- Children 2 to 6 years: Use only a pea sized amount and supervise child's brushing and rinsing (to minimize swallowing).
- Children under 2 years: Ask a dentist or physician.

Inactive ingredients

sorbitol, water, hydrated silica, PEG-12, sodium lauryl sulfate, flavor, cellulose gum, tetrasodium pyrophosphate, cocamidopropyl betaine, sodium saccharin, titanium dioxide, FD&C blue no. 1, FD&C yellow no. 5

Questions or comments?

1-800-468-6502

Dist. by:
COLGATE-PALMOLIVE COMPANY
New York, NY 10022
Made in Canada
www.colgate.com

PRINCIPAL DISPLAY PANEL - 130 g Tube

Colgate®
Fluoride Toothpaste

NET WT 4.6 OZ (130 g)

Triple
Action

Original Mint

Cavity Protection
1

Whiter Teeth
2

Fresh Breath
3